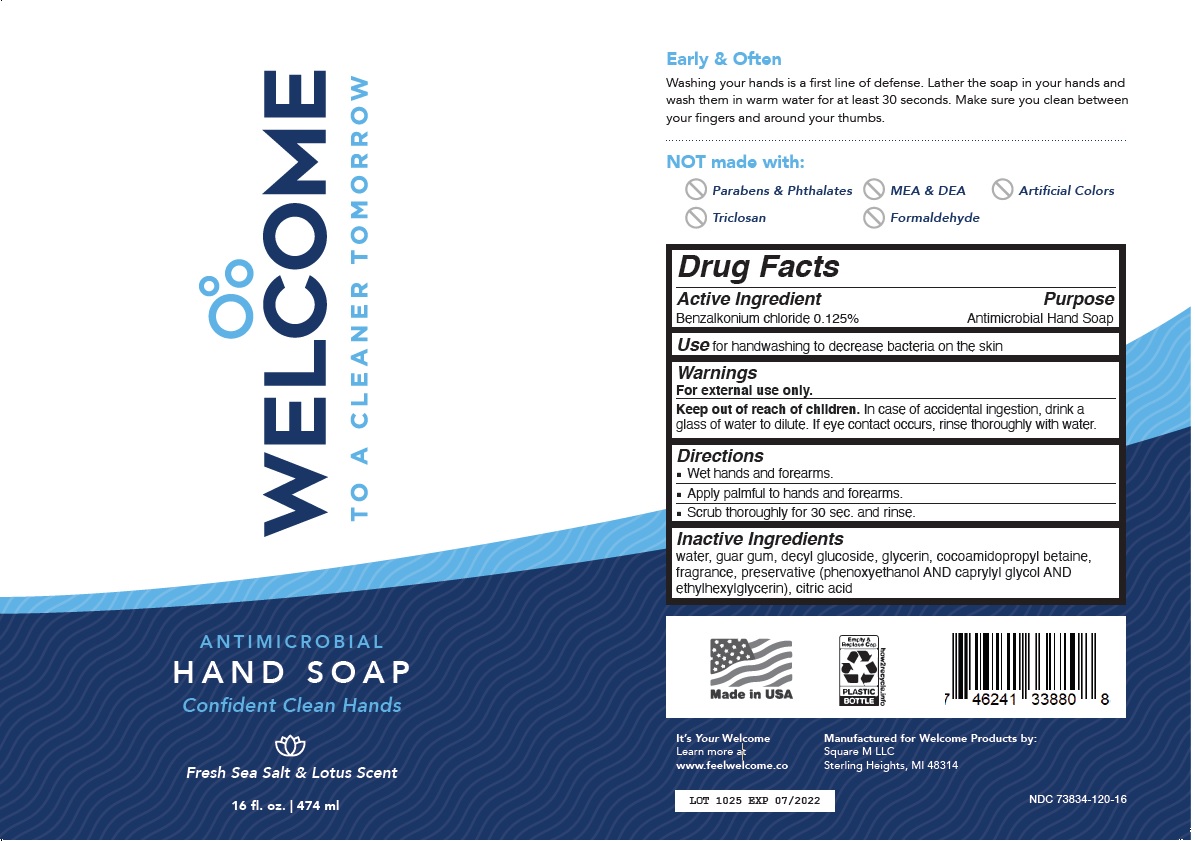 DRUG LABEL: WELCOME ANTIMICROBIAL HANDSOAP
NDC: 73834-120 | Form: LIQUID
Manufacturer: Square M Llc
Category: otc | Type: HUMAN OTC DRUG LABEL
Date: 20201130

ACTIVE INGREDIENTS: BENZALKONIUM CHLORIDE 0.125 g/100 mL
INACTIVE INGREDIENTS: WATER; GUAR GUM; DECYL GLUCOSIDE; GLYCERIN; COCAMIDOPROPYL BETAINE; PHENOXYETHANOL; CAPRYLYL GLYCOL; ETHYLHEXYLGLYCERIN; CITRIC ACID MONOHYDRATE

WELCOME ANTIMICROBIAL HAND SOAP

Active Ingredient

Benzalkonium chloride 0.125%

Purpose

Antimicrobial Hand Soap

INDICATIONS AND USAGE

Use for handwashing to decrease bacteria on the skin

Warnings

For external use only.

Keep out of reach of children. In case of accidental ingestion, drink a glass of water to dilute. If eye contact occurs, rinse thoroughly with water.

Directions

■ Wet hands and forearms.

■ Apply palmful to hands and forearms.

■ Scrub thoroughly for 30 sec. and rinse.

Inactive Ingredients

water, guar gum, decyl glucoside, glycerin, cocoamidopropyl betaine, fragrance, preservative (phenoxyethanol AND caprylyl glycol AND ethylhexylglycerin), citric acid

TO A CLEANER TOMORROW

Confident Clean Hands

Fresh Sea Salt & Lotus Scent

Early & Often

Washing your hands is a first line of defense. Lather the soap in your hands and wash them in warm water for at least 30 seconds. Make sure you clean between your fingers and around your thumbs.

NOT made with:

- Parabens & Phthalates
- Triclosan
- MEA & DEA
- Formaldehyde
- Artificial Colors

Made in USA

It’s Your Welcome

Learn more at

www.feelwelcome.co

Manufactured for Welcome Products by:

Square M LLC

Sterling Heights, MI 48314